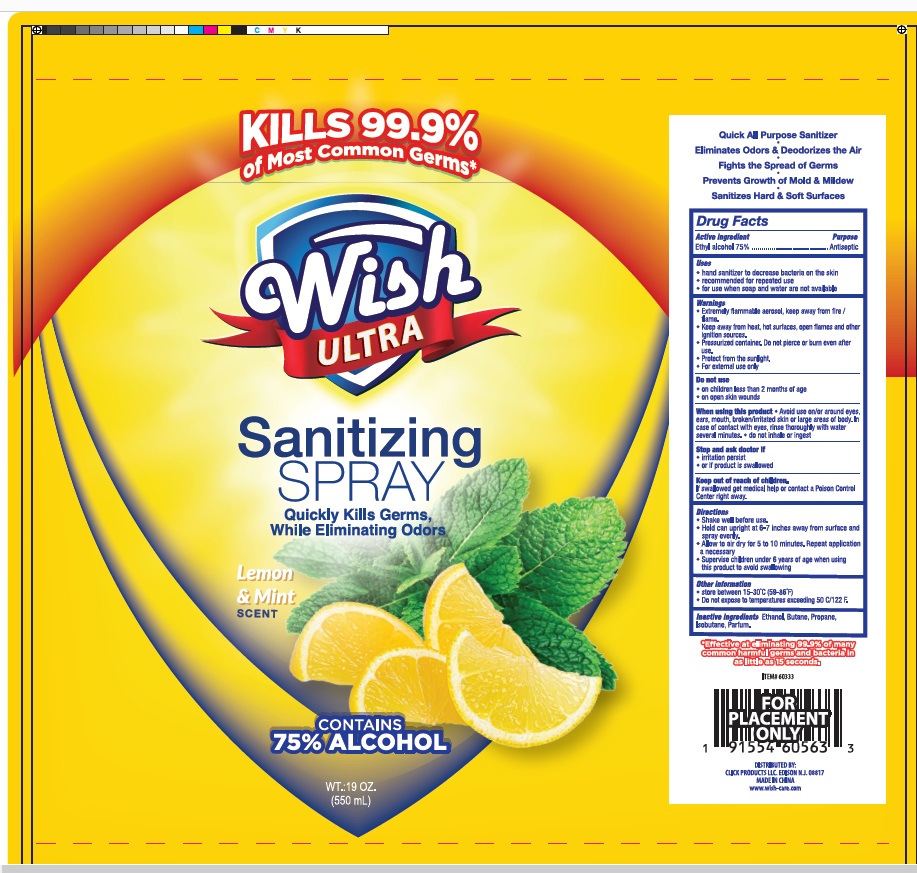 DRUG LABEL: WISH ULTRA ALCOHOL SANITIZING
NDC: 71611-018 | Form: SPRAY
Manufacturer: Click Products LLC
Category: otc | Type: HUMAN OTC DRUG LABEL
Date: 20200929

ACTIVE INGREDIENTS: ALCOHOL 75 mL/100 mL
INACTIVE INGREDIENTS: ISOBUTANE; PROPANE; BUTANE

WISH ULTRA ALCOHOL SANITIZING SPRAY: LEMON AND MINT

Active Ingredients

Ethyl Alcohol 75%

Purpose

Antiseptic

Uses

-hand sanitizer to decrease bacteria on the skin

-recommended for repeated use

-for use when soap and water are not available

WARNINGS

-Flammable.Keep away from heat and flame/fire

-Keep away from heat, hot surfaces, open flames and ignition sources

-Pressurized container. Do not pierce or burn even after use

-Protect from sunlight

-For external use only

DO NOT USE

-On children less than 2 months of age

-On open skin wounds

WHEN USING

-Avoid use on/or around eyes, ears, mouth, broken/irritated skin or large areas of body. in case of contact with eyes, rinse thoroughly with water several minutes.

- Do not inhale

STOP USE

-irritation persist

-if product is swallowed

KEEP OUT OF REACH OF CHILDREN

If swallowed get medical help or contact a poison control center right away

Directions

-Shake well before use.

-Hold can upright at 6-7 inches away from the surface and spray evenly.

-Allow to air dry for 5 to 10 minutes. Repeat application a necessary.

-Supervise children under 6 years of age when using this product to avoid swallowing.

STORAGE AND HANDLING

-store between 15-30 degree Celcius

-Do not expose to temperature exceeding 50 degree celcius

INACTIVE INGREDIENT

Ethanol, Butane, Propane, Isobutane, Parfum.